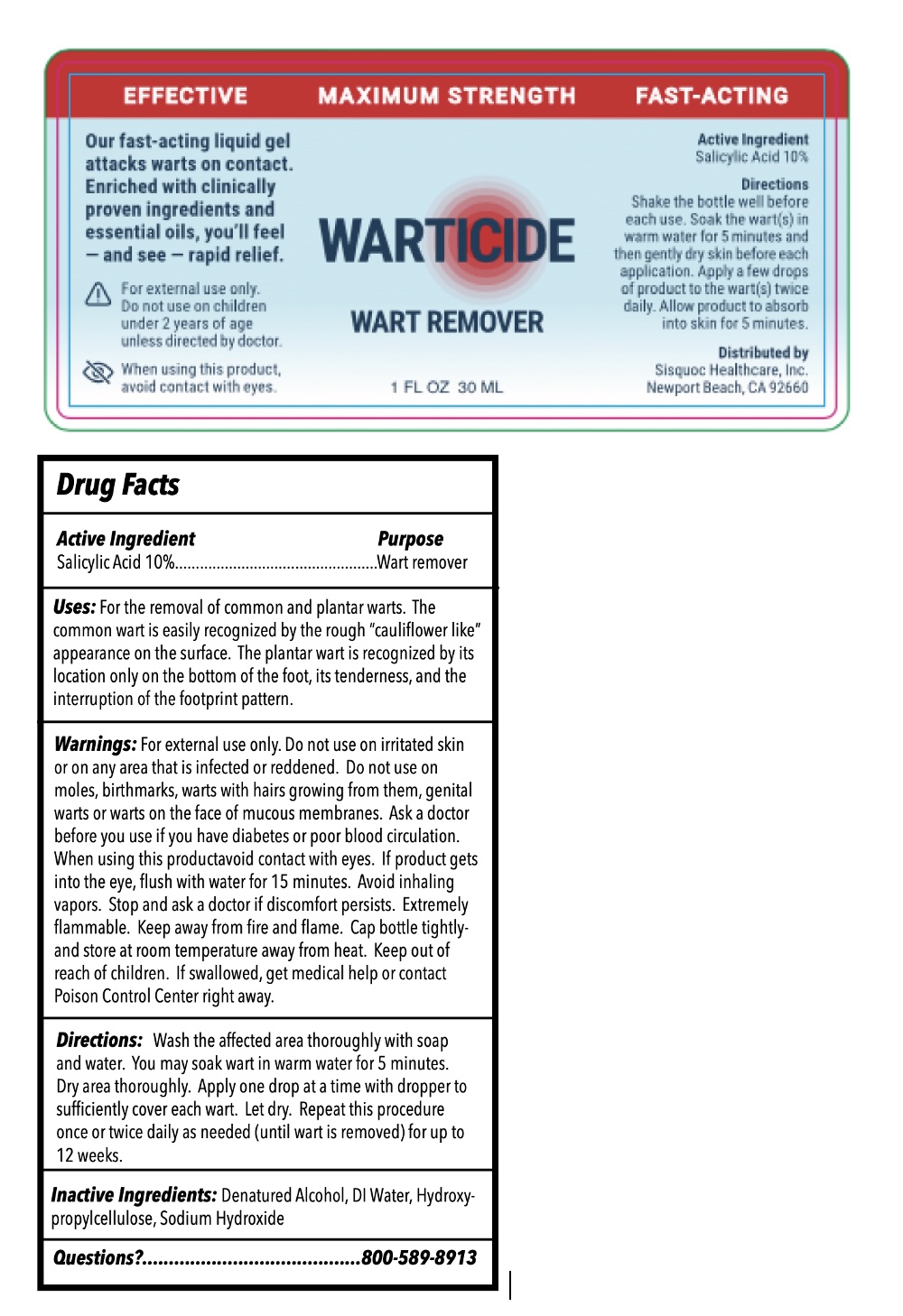 DRUG LABEL: WARTICIDE
NDC: 71229-105 | Form: SOLUTION
Manufacturer: The Sisquoc Healthcare Corporation
Category: otc | Type: HUMAN OTC DRUG LABEL
Date: 20250421

ACTIVE INGREDIENTS: SALICYLIC ACID 10 g/100 mL
INACTIVE INGREDIENTS: WATER; ALCOHOL; XANTHAN GUM; TEA TREE OIL; CEDAR LEAF OIL

Sisquoc HC - WARTICIDE (71229-105)

ACTIVE INGREDIENT

SALICYLIC ACID 10%

PURPOSE

WART REMOVER

USES

- WART REMOVER

WARNINGS

FOR EXTERNAL USE ONLY.

DO NOT USE ON CHILDREN UNDER 2 YEARS OF AGE UNLESS DIRECTED BY A DOCTOR.

WHEN USING THIS PRODUCT AVOID CONTACT WITH THE EYES. IF CONTACT OCCURS, RINSE THE EYES VERY THOROUGHLY WITH WATER.

STOP USE AND ASK A DOCTOR IF IRRITATION OCCURS OR THERE IS NO IMPROVEMENT WITHIN 4 WEEKS.

KEEP OUT OF REACH OF CHILDREN. IF SWALLOWED, GET MEDICAL HELP OR CONTACT A POISON CONTROL CENTER RIGHT AWAY.

DIRECTIONS

Simply unscrew the top and fill the dropper tip with liquid. Once full, apply Warticide to the wart or warts until the infected area is lightly covered with gel. Gently work Warticide into the wart with a finger and then wash hands after application is finished. Allow 3-4 minutes for the solution to absorb.

INACTIVE INGREDIENTS

WATER, ETHANOL, XANTHAN GUM, MELALEUCA ALTERNIFOLIA LEAF OIL, CEDAR LEAF OIL.

STORAGE AND HANDLING

Store between 20°c to 25°C (68° to 77°F)